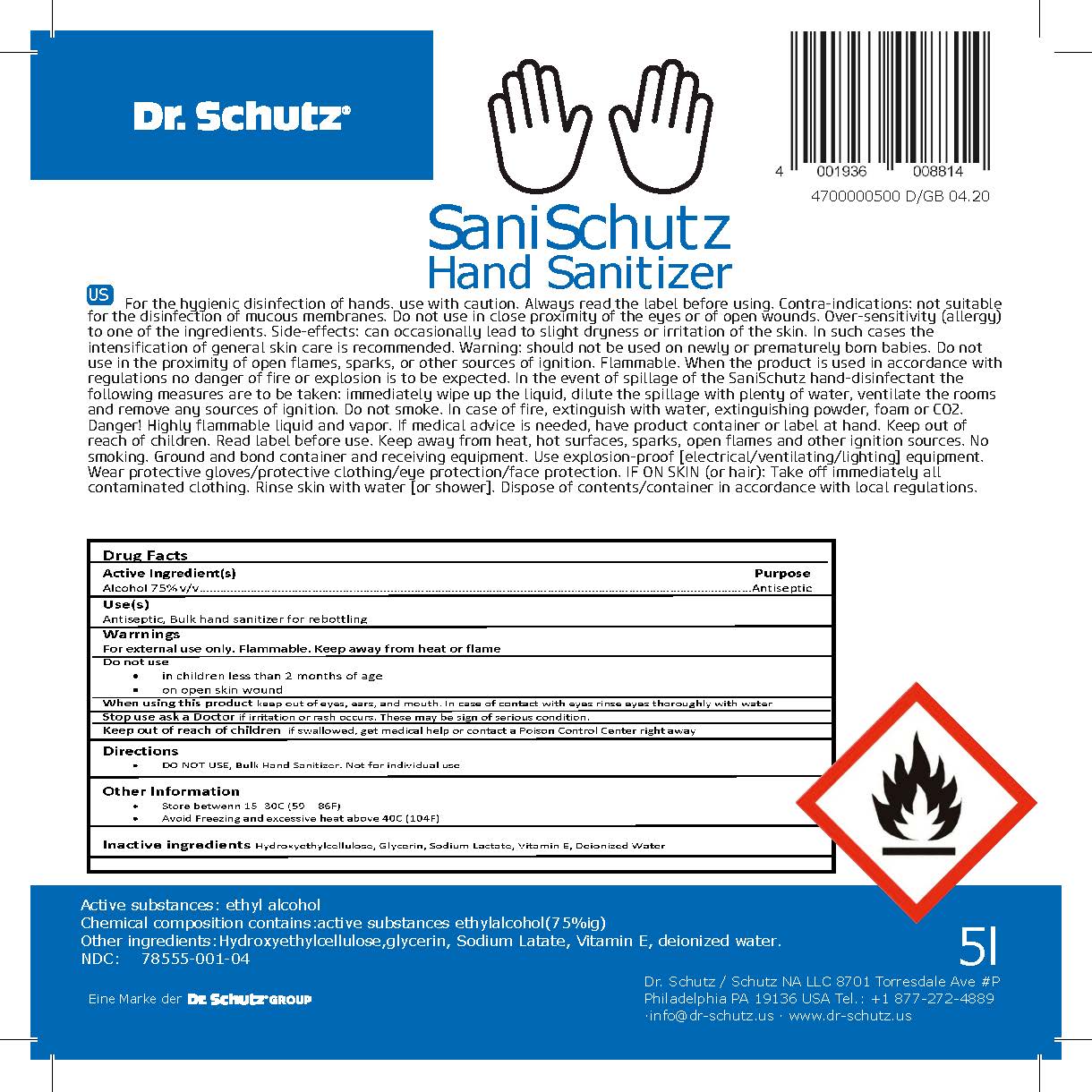 DRUG LABEL: Sani Schutz
NDC: 78555-001 | Form: SOLUTION
Manufacturer: Schutz NA LLC
Category: otc | Type: HUMAN OTC DRUG LABEL
Date: 20200608

ACTIVE INGREDIENTS: ALCOHOL 75 mL/100 mL
INACTIVE INGREDIENTS: WATER 21.267 mL/100 mL; HYDROXYETHYL CELLULOSE, UNSPECIFIED 2.233 mL/100 mL; GLYCERIN .56 mL/100 mL; SODIUM LACTATE .50 mL/100 mL; ALPHA-TOCOPHEROL ACETATE .44 mL/100 mL

Hand Sanitizer Gel

The hand rub is manufactured using only the following United States Pharmacopoeia (USP) grade ingredients in the preparation of the product (percentage in final product formulation) consistent with World Health Organization (WHO) recommendations:

1. Alcohol (ethanol) (USP or Food Chemical Codex (FCC) grade) (75%, volume/volume (v/v)) in an aqueous solution denatured according to Alcohol and Tobacco Tax and Trade Bureau regulations in 27 CFR part 20.
2. Glycerol (0.56% v/v).
3. Hydroxyethylcellulose (2.23% v/v).
4. Sodium Lactate (0.50% v/v).
5. Vitamin E (0.44% v/v)
6. Sterile distilled water or boiled cold water.

The firm does not add other active or inactive ingredients. Different or additional ingredients may impact the quality and potency of the product.

Active Ingredient(s)

Alcohol 75% v/v. Purpose: Antiseptic

Purpose

Antiseptic, Hand Rub

Use

Health care personnel hand rub to help reduce bacteria that potentially can cause disease.

Warnings

For external use only. Flammable. Keep away from heat or flame

Do not use

- in children less than 2 months of age
- on open skin wounds

When using this product keep out of eyes, ears, and mouth. In case of contact with eyes, rinse eyes thoroughly with water.
Stop use and ask a doctor if irritation or rash occurs. These may be signs of a serious condition.
Keep out of reach of children. If swallowed, get medical help or contact a Poison Control Center right away.

Stop use and ask a doctor if irritation or rash occurs. These may be signs of a serious condition.

Keep out of reach of children. If swallowed, get medical help or contact a Poison Control Center right away.

Directions

- Place enough product on hands to cover all surfaces. Rub hands together until dry.
- Supervise children under 6 years of age when using this product to avoid swallowing.

Other information

- Store between 15-30C (59-86F)
- Avoid freezing and excessive heat above 40C (104F)

Inactive ingredients

glycerin, hydroxyethylcellulose, vitamin e, purified water

Package Label - Principal Display Panel

5 L (5000 mL) NDC: 78555-001-04